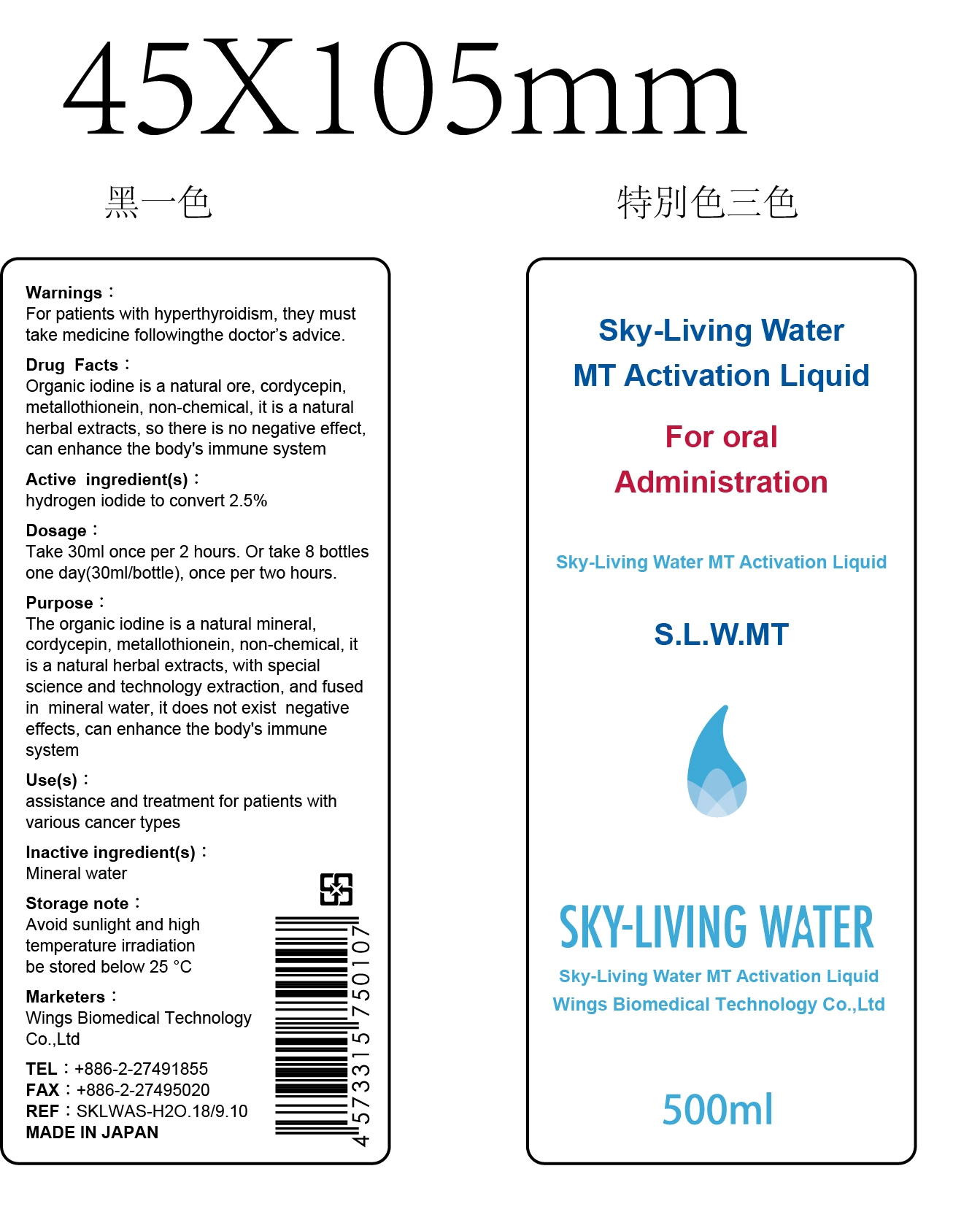 DRUG LABEL: Sky-Living Water MT Activition Liquid
NDC: 70148-001 | Form: LIQUID
Manufacturer: WINGS BIOMEDICAL TECHNOLOGY CO., LTD.
Category: prescription | Type: HUMAN PRESCRIPTION DRUG LABEL
Date: 20151020

ACTIVE INGREDIENTS: IODINE 2.5 g/100 mL
INACTIVE INGREDIENTS: WATER

Drug fact

Active Ingredient: Hydrogen Iodine to convert 2.5%

WARNINGS

For patients with hyperthyroidism, they must take medicine following doctor's advice.

Dosage:

Take 30 mL per two hours, or take 8 bottles one day (30 mL per bottle), once per two hours

Purpose:

The organic iodine is a natural mineral, cordycepin, metallothionein, non-chemical, it is a batural herbel extract, with special science and technology extraction, and fused in mineral water, it does not exist negative effect, can enhance the body's immune system.

Uses:

Assistance and treatment for patients with various cancer types

Inactive Ingradient:

Mineral water

Storage:

Avoid sunlight and high temperature irridiation, be stored below 25C